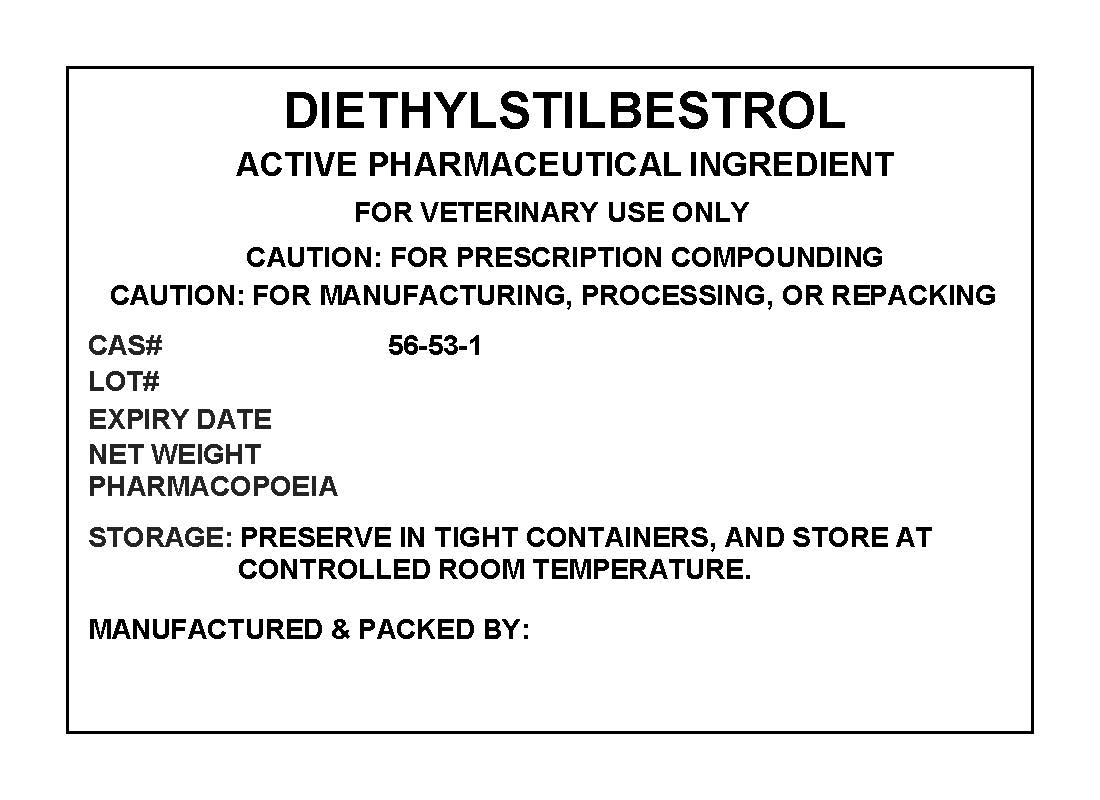 DRUG LABEL: DIETHYLSTILBESTROL
NDC: 72969-080 | Form: POWDER
Manufacturer: PROFESSIONAL GROUP OF PHARMACISTS NEW YORK LLC
Category: other | Type: BULK INGREDIENT
Date: 20210311

ACTIVE INGREDIENTS: DIETHYLSTILBESTROL 1 g/1 g

DIETHYLSTILBESTROL

PACKAGE LABEL

diethylstilbestrollabel.jpg